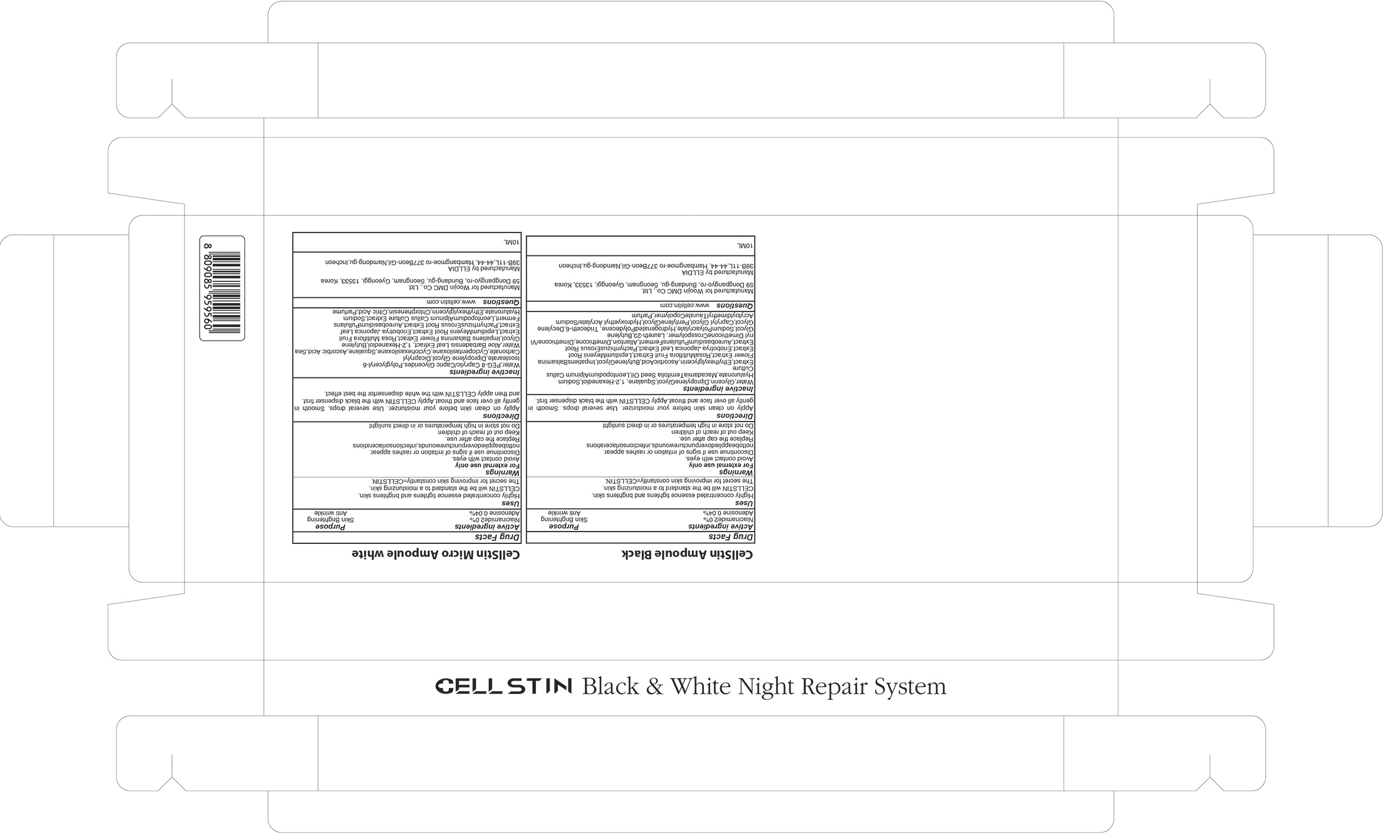 DRUG LABEL: CellStin Ampoule Black
NDC: 72049-010 | Form: LIQUID
Manufacturer: Woojin DMC Co.,Ltd.
Category: otc | Type: HUMAN OTC DRUG LABEL
Date: 20180129

ACTIVE INGREDIENTS: Niacinamide 0.2 g/10 mL; Adenosine 0.004 g/10 mL
INACTIVE INGREDIENTS: Water; Glycerin

ACTIVE INGREDIENT

Active ingredients: Niacinamide 2.0%, Adenosine 0.04%

INACTIVE INGREDIENT

Inactive ingredients: Water,Glycerin,Dipropylene Glycol,Squalane, 1,2-Hexanediol,Sodium Hyaluronate,Macadamia Ternifolia Seed Oil, Leontopodium Alpinum Callus Culture Extract,Ethylhexylglycerin,Ascorbic Acid,Butylene Glycol,Impatiens Balsamina Flower Extract,Rosa Multiflora Fruit Extract,Lepidium Meyenii Root Extract,Eriobotrya Japonica Leaf Extract,Pachyrrhizus Erosus Root Extract,Aureobasidium Pullulans Ferment,Allantoin,Dimethicone,Dimethicone/Vinyl Dimethicone Crosspolymer, Laureth-23,Butylene Glycol,Sodium Polyacrylate,Hydrogenated Polydecene, Trideceth-6,Decylene Glycol,Caprylyl Glycol, Pentylene Glycol,Hydroxyethyl Acrylate/Sodium Acryloyldimethyl Taurate Copolymer,Parfum

PURPOSE

Purpose: Skin Brightening, Anti wrinkle

WARNINGS

Warnings: For external use only Avoid contact with eyes. Discontinue use if signs of irritation or rashes appear. not to be applied over puncture wounds, infections or lacerations Replace the cap after use. Keep out of reach of children Do not store in high temperatures or in direct sunlight

KEEP OUT OF REACH OF CHILDREN

Uses

Uses: Highly concentrated essence tightens and brightens skin. CELLSTIN will be the standard to a moisturizing skin. The secret for improving skin constantly=CELLSTIN.

Directions

Directions: Apply on clean skin before your moisturizer. Use several drops. Smooth in gently all over face and throat. Apply CELLSTIN with the black dispenser first.